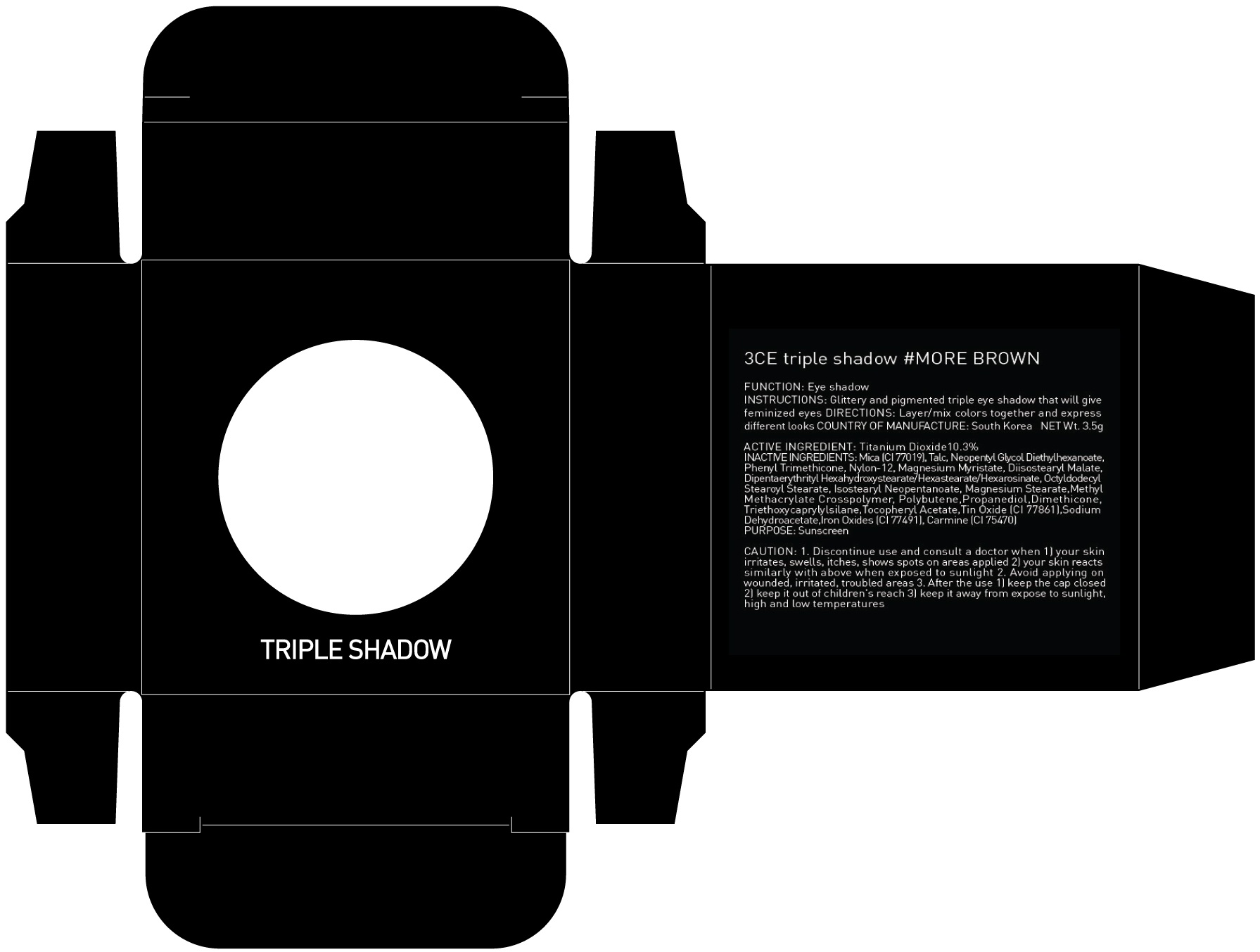 DRUG LABEL: 3CE TRIPLE SHADOW MORE BROWN
NDC: 60764-024 | Form: POWDER
Manufacturer: Nanda Co., Ltd
Category: otc | Type: HUMAN OTC DRUG LABEL
Date: 20160922

ACTIVE INGREDIENTS: Titanium Dioxide 0.36 g/3.5 g
INACTIVE INGREDIENTS: Mica; Talc

ACTIVE INGREDIENT

Active Ingredient: Titanium Dioxide 10.3%

INACTIVE INGREDIENT

Inactive Ingredients: Mica (CI 77019), Talc, Neopentyl Glycol Diethylhexanoate, Phenyl Trimethicone, Nylon-12, Magnesium Myristate, Diisostearyl Malate, Dipentaerythrityl Hexahydroxystearate/Hexastearate/Hexarosinate, Octyldodecyl Stearoyl Stearate, Isostearyl Neopentanoate, Magnesium Stearate,Methyl Methacrylate Crosspolymer, Polybutene,Propanediol,Dimethicone, Triethoxycaprylylsilane,Tocopheryl Acetate,Tin Oxide (CI 77861),Sodium Dehydroacetate,Iron Oxides (CI 77491), Carmine (CI 75470)

PURPOSE

Purpose: Sunscreen

CAUTION

CAUTION: 1. Discontinue use and consult a doctor when - your skin irritates, swells, itches, shows spots on areas applied - your skin reacts similarly with above when exposed to sunlight 2. Avoid applying on wounded, irritated, troubled areas 3. After the use - keep the cap closed - keep it out of children's reach - keep it away from expose to sunlight, high and low temperatures

DESCRIPTION

INSTRUCTIONS: Glittery and pigmented triple eye shadow that will give feminized eyes.

Directions: Layer/mix colors together and express different looks